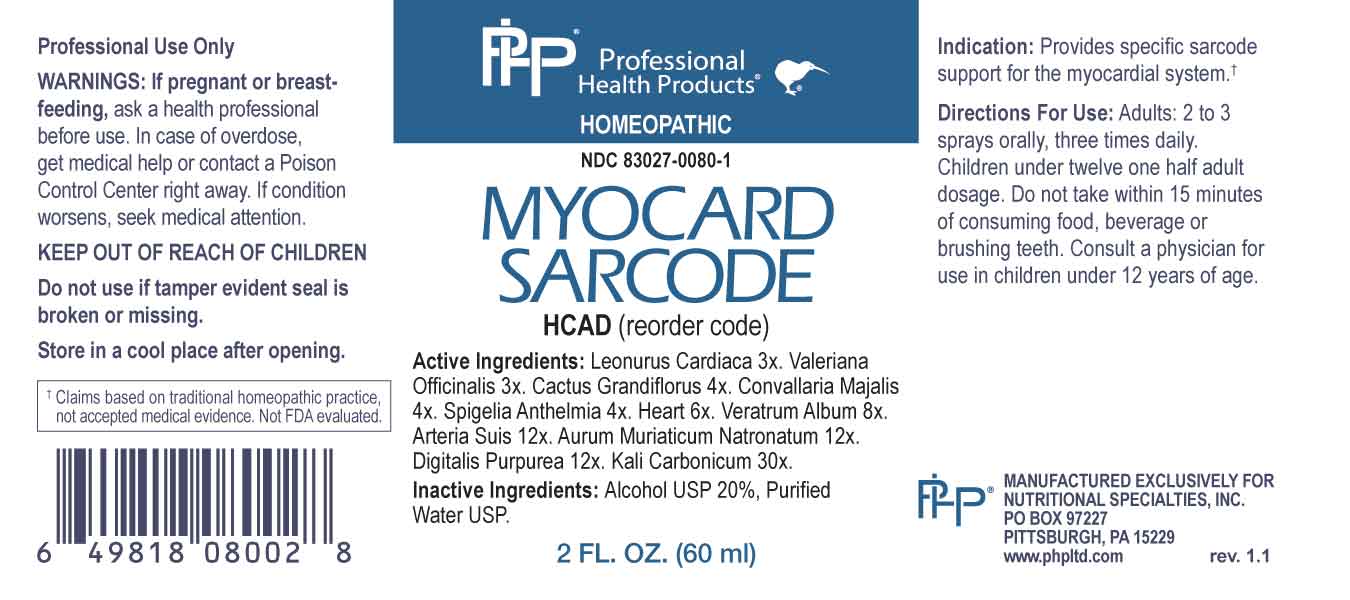 DRUG LABEL: Myocard Sarcode
NDC: 83027-0080 | Form: SPRAY
Manufacturer: Nutritional Specialties, Inc.
Category: homeopathic | Type: HUMAN OTC DRUG LABEL
Date: 20230927

ACTIVE INGREDIENTS: LEONURUS CARDIACA WHOLE 3 [hp_X]/1 mL; VALERIAN 3 [hp_X]/1 mL; SELENICEREUS GRANDIFLORUS STEM 4 [hp_X]/1 mL; CONVALLARIA MAJALIS 4 [hp_X]/1 mL; SPIGELIA ANTHELMIA WHOLE 4 [hp_X]/1 mL; BEEF HEART 6 [hp_X]/1 mL; VERATRUM ALBUM ROOT 8 [hp_X]/1 mL; SUS SCROFA ARTERY 12 [hp_X]/1 mL; SODIUM TETRACHLOROAURATE 12 [hp_X]/1 mL; DIGITALIS 12 [hp_X]/1 mL; POTASSIUM CARBONATE 30 [hp_X]/1 mL
INACTIVE INGREDIENTS: WATER; ALCOHOL

DRUG FACTS:

ACTIVE INGREDIENTS:

Leonurus Cardiaca 3X, Valeriana Officinalis 3X, Cactus Grandiflorus 4X, Convallaria Majalis 4X, Spigelia Anthelmia 4X, Heart 6X, Veratrum Album 8X, Arteria Suis 12X, Aurum Muriaticum Natronatum 12X, Digitalis Purpurea 12X, Kali Carbonicum 30X.

PURPOSE:

Provides specific sarcode support for the myocardial system.†

†Claims based on traditional homeopathic practice, not accepted medical evidence. Not FDA evaluated.

WARNINGS:

Professional Use Only

If pregnant or breast-feeding, ask a health professional before use.

In case of overdose, get medical help or contact a Poison Control Center right away.

If condition worsens, seek medical attention.

KEEP OUT OF REACH OF CHILDREN

Do not use if tamper evident seal is broken or missing.

Store in a cool place after opening

KEEP OUT OF REACH OF CHILDREN:

In case of overdose, get medical help or contact a Poison Control Center right away.

DIRECTIONS:

Adults: 2 to 3 sprays orally, three times daily. Children under twelve one half adult dosage. Do not take within 15 minutes of consuming food, beverage or brushing teeth. Consult a physician for use in children under 12 years of age.

INDICATIONS:

Provides specific sarcode support for the myocardial system.†

†Claims based on traditional homeopathic practice, not accepted medical evidence. Not FDA evaluated.

INACTIVE INGREDIENTS:

Alcohol USP 20%, Purified Water USP.

QUESTIONS:

MANUFACTURED EXCLUSIVELY FOR

NUTRITIONAL SPECIALTIES, INC.

PO BOX 97227

PITTSBURG, PA 15229

www.phpltd.com

PACKAGE LABEL DISPLAY:

Professional

Health Products

HOMEOPATHIC

NDC 83027-0080-1

MYOCARD

SARCODE

2 FL. OZ (60 ml)